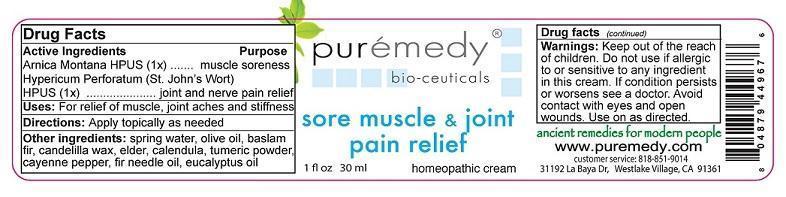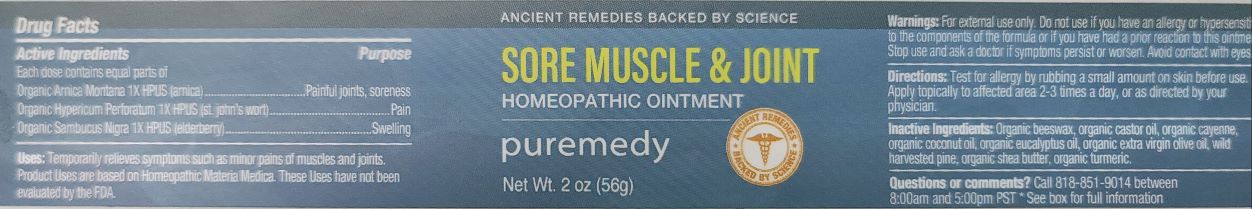 DRUG LABEL: SORE MUSCLE AND JOINT PAIN RELIEF
NDC: 52810-703 | Form: CREAM
Manufacturer: PUREMEDY
Category: homeopathic | Type: HUMAN OTC DRUG LABEL
Date: 20240111

ACTIVE INGREDIENTS: ARNICA MONTANA 1 [hp_X]/100 mL; HYPERICUM PERFORATUM 1 [hp_X]/100 mL
INACTIVE INGREDIENTS: WATER; OLIVE OIL; ABIES BALSAMEA LEAF OIL; CANDELILLA WAX; SAMBUCUS NIGRA FLOWER; CALENDULA OFFICINALIS SEED OIL; TURMERIC; CAPSICUM; EUCALYPTUS OIL

SORE MUSCLE AND JOINT RELIEF (52810-703)

ACTIVE INGREDIENTS

ARNICA MONTANA HPUS (1X)

HYPERICUM PERFORATUM (ST. JOHN'S WORT) HPUS (1X)

PURPOSE

MUSCLE SORENESS

JOINT AND NERVE PAIN RELIEF

INDICATIONS AND USAGE

USES: FOR RELIEF OF MUSCLE, JOINT ACHES AND STIFFNESS

DOSAGE AND ADMINISTRATION

DIRECTIONS: APPLY TOPICALLY AS NEEDED.

INACTIVE INGREDIENT

OTHER INGREDIENTS: SPRING WATER, OLIVE OIL, BALSAM FIR, CANDELILA WAX, ELDER, CALENDULA, TUMERIC POWDER, CAYENNE PEPPER, FIR NEEDLE OIL, EUCALYPTUS OIL

WARNINGS

WARNING: DO NOT USE IF ALLERGIC TO OR SENSITIVE TO ANY INGREDIENT IN THIS CREAM. IF CONDITION PERSISTS OR WORSENS SEE A DOCTOR. AVOID CONTACT WITH EYES AND OPEN WOUNDS. USE ONLY AS DIRECTED.

KEEP OUT OF REACH OF CHILDREN.